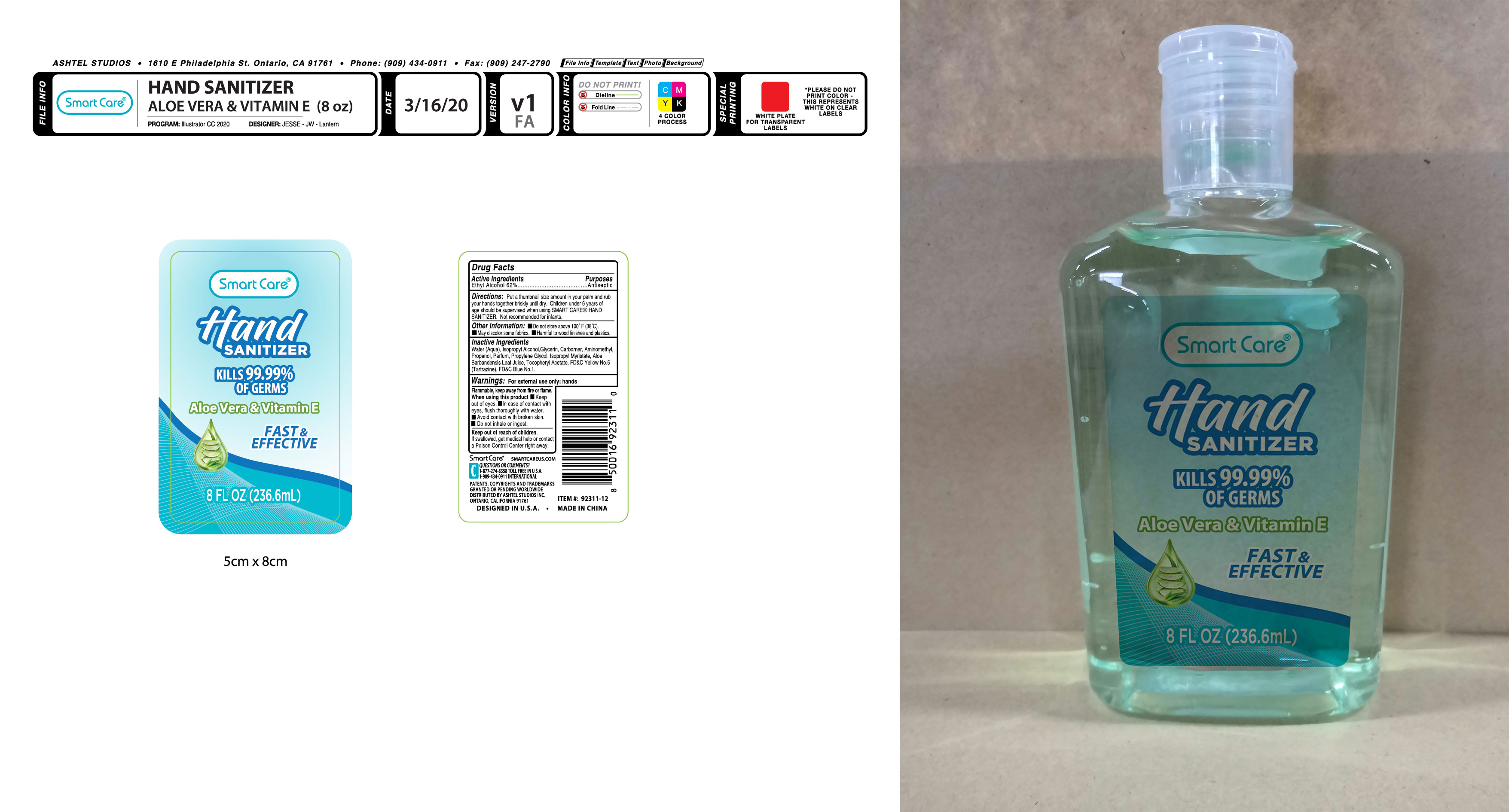 DRUG LABEL: Smart Care Hand Sanitizer 8oz
NDC: 54860-409 | Form: LIQUID
Manufacturer: Shenzhen Lantern Science Co.,Ltd.
Category: otc | Type: HUMAN OTC DRUG LABEL
Date: 20230512

ACTIVE INGREDIENTS: ALCOHOL 62 mL/100 mL
INACTIVE INGREDIENTS: ALOE VERA LEAF 0.1 mL/100 mL; ALOE 0.15 mL/100 mL; ISOPROPYL MYRISTATE 0.001 mL/100 mL; CARBOMER 940 0.26 mL/100 mL; WATER 36.307916 mL/100 mL; ISOPROPYL ALCOHOL 0.5 mL/100 mL; FD&C YELLOW NO. 5 0.00006 mL/100 mL; AMINOMETHYLPROPANOL 0.08 mL/100 mL; FD&C BLUE NO. 1 0.000024 mL/100 mL; GLYCERIN 0.5 mL/100 mL; PROPYLENE GLYCOL 0.1 mL/100 mL; .ALPHA.-TOCOPHEROL ACETATE 0.001 mL/100 mL

Smart Care Hand Sanitizer 8oz

Medicical Ingredient

Medicical Ingredient Purpose

Ethyl Alcohol 62% Antiseptic

Features

To decrease bacteria on the skin that could cause disease.

DOSAGE AND ADMINISTRATION

Recommended for repeated use.

use anywhere without water.

Warning

For extenal use only:hands.

Flammable,Keep away from fire or flame.

WARNINGS AND PRECAUTIONS

For external use only.

Flammable, keep away from heat and flame.

STOP USE

Discontinue if skin becomes irritated and ask a doctor .

Keep out of reach of children. In case of accidental ingestion, seek professional assistance or contact a poson control center immediately.

Non-Medicinal

Alcohol，Aqua(water)，Isopropyl Alcohol，Glycerin，Carbomer，Aminomethyl Propanol，Parfum，Propylene Glycol，ISOPROPYL MYRISTATE，ALOE BARBADENSIS LEAF JUICE，Tocopheryl Acetate，YELLOW 5，BLUE 1

Directions

Wet hands thoroughly with product and rub until dry without wiping

For children under 6, use only under adult supervision.

Not recommended for infants.

When using this product

keep out of eyes. In case of contact with eyes, flush thoroughly with water.

Do not inhale or ingest.

Avoid contact with broken skin.

Other information

Do not store above 105F.

May discolor some fabrics.

Harmful to wood finishes and plastics.